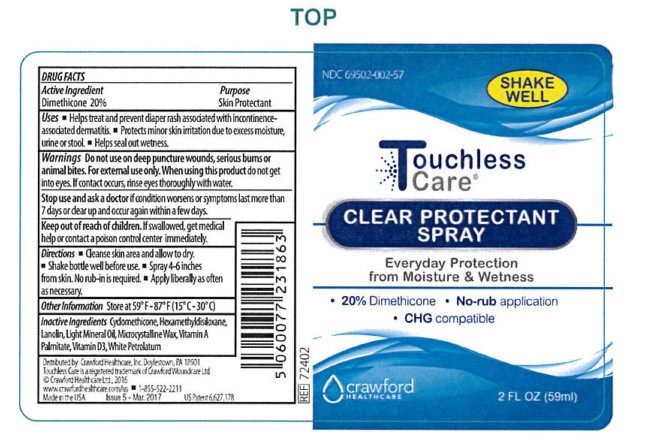 DRUG LABEL: Touchless Care CLEAR PROTECTANT
NDC: 69502-002 | Form: SPRAY
Manufacturer: Crawford Healthcare, Inc.
Category: otc | Type: HUMAN OTC DRUG LABEL
Date: 20170412

ACTIVE INGREDIENTS: DIMETHICONE 20 g/100 g
INACTIVE INGREDIENTS: MINERAL OIL; CYCLOMETHICONE; PETROLATUM; MICROCRYSTALLINE WAX; LANOLIN; HEXAMETHYLDISILOXANE; VITAMIN A PALMITATE; CHOLECALCIFEROL

Touchless Care CLEAR PROTECTANT SPRAY

Active Ingredient

Dimethicone 20%

Purpose

Skin Protectant

Uses

- Helps treat and prevent diaper rash associated with incontinence-associated dermatitis
- Protects minor skin irritation due to excess moisture, urine or stool
- Helps seal out wetness.

Warnings

Do not use on deep puncture wounds, serious burns or animal bites. For external use only. When using this product do not get into eyes. If contact occurs, rinse eyes thoroughly with water.

Stop use and ask a doctor if

condition worsens or symptoms last more than 7 days or clear up and occur again within a few days.

Keep out of reach of children

If swallowed, get medical help or contact a poison control center immediately.

Directions

- Cleanse skin area and allow to dry.
- Shake bottle well before use.
- Spray 4-6 inches from skin. No rub-in is required.
- Apply liberally as often as necessary.

Other Information

Store at 59oF - 87oF (15oC - 30oC)

Inactive Ingredients

Cyclomethicone, Hexamethyldisiloxane, Lanolin, Light Mineral Oil, Microcrystalline Wax, Vitamin A Palmitate, Vitamin D3, White Petrolatum

SPL Unclassified Section

Distributed by: Crawford Healthcare, Inc. Doylestown, PA 18901

Touchless Care is a registered trademark of Crawford Woundcare Ltd.

© Crawford Healthcare Ltd., 2016

www.crawfordhealthcare.com/us

1-855-522-2211

Made in the USA